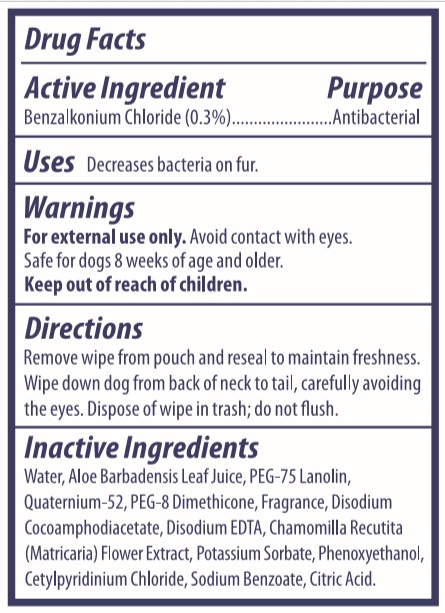 DRUG LABEL: Antibacterial Mulit-purpose Wipes
NDC: 77720-004 | Form: CLOTH
Manufacturer: Skaffles Group Limited Liability Company
Category: animal | Type: OTC ANIMAL DRUG LABEL
Date: 20200729

ACTIVE INGREDIENTS: BENZALKONIUM CHLORIDE 0.3 g/100 g
INACTIVE INGREDIENTS: WATER; QUATERNIUM-52; PEG-75 LANOLIN; ALOE VERA LEAF; CITRIC ACID MONOHYDRATE; CETYLPYRIDINIUM CHLORIDE; PEG-8 DIMETHICONE; DISODIUM COCOAMPHODIACETATE; DISODIUM EDTA-COPPER; CHAMOMILE; POTASSIUM SORBATE; PHENOXYETHANOL; SODIUM BENZOATE

Active Ingredient

Benzalkonium Chloride 0.3%

Purpose

Antibacterial

USE

Decreases Bacteria on fur

Warning

For external use only.

Avoid Contact with eyes. Safe for dogs 8 weeks of age and older.

Keep out of reach of children.

Directions

Remove wipe from pouch and reseal to maintain freshness,

wipe down dog from back of neck to tail,carefully avoiding the eyes ,didpose of wipe in trash ,do not flush

Inactive ingredients

Inactive ingredients Water, Aloe Barbadensis Leaf Juice,
PEG-75 Lanolin, Quatermium-52, PEG-8 Dimethicone, Disodium
Cocoamphodiacetate, Disodium EDTA, Chamomilla Recutita
(Matricaria) Flower Extract, Potassium Sorbate, Phenoxyethanol,
Cetylpyridinium Chloride, Sodium Benzoate, Citric Acid.